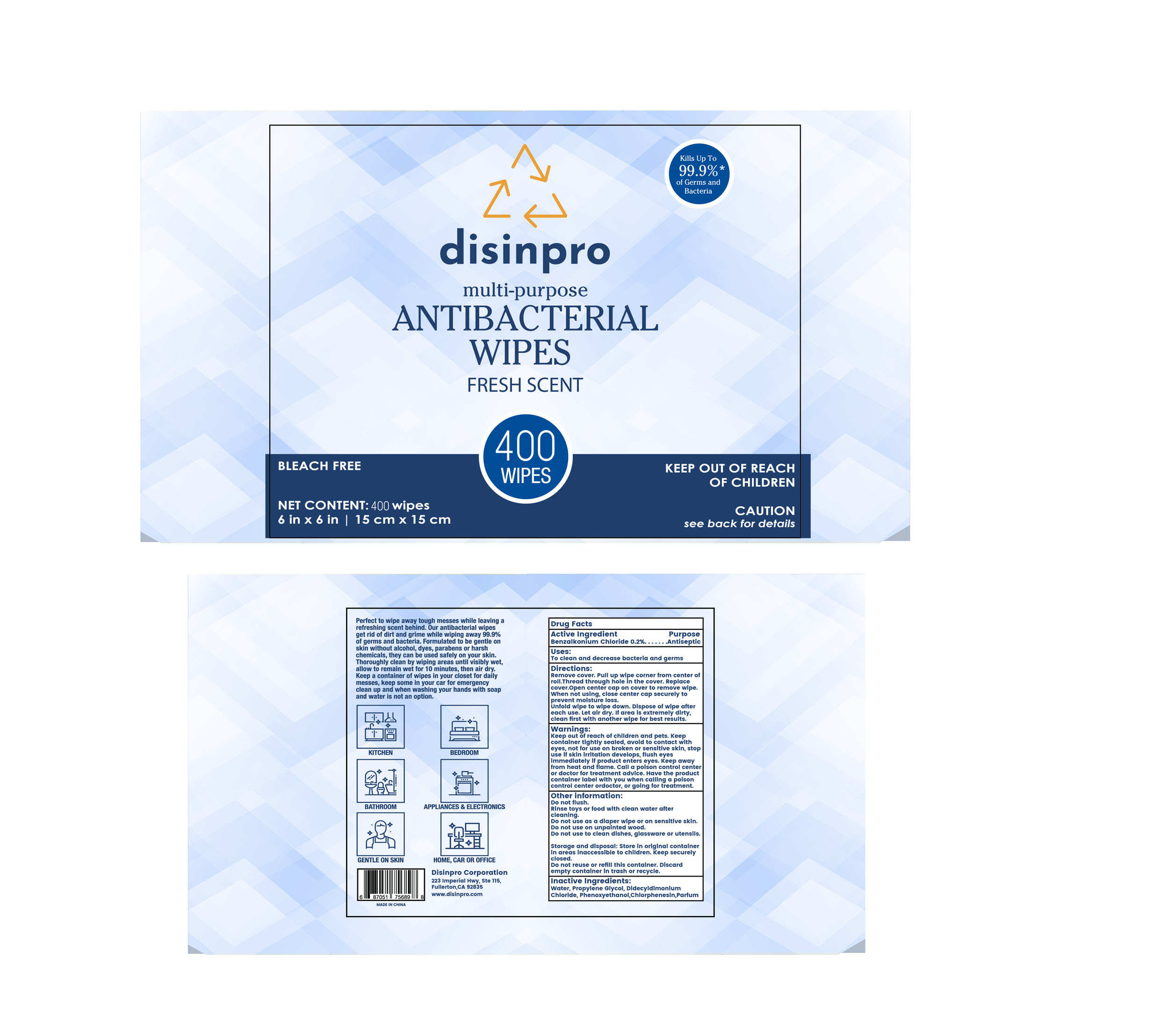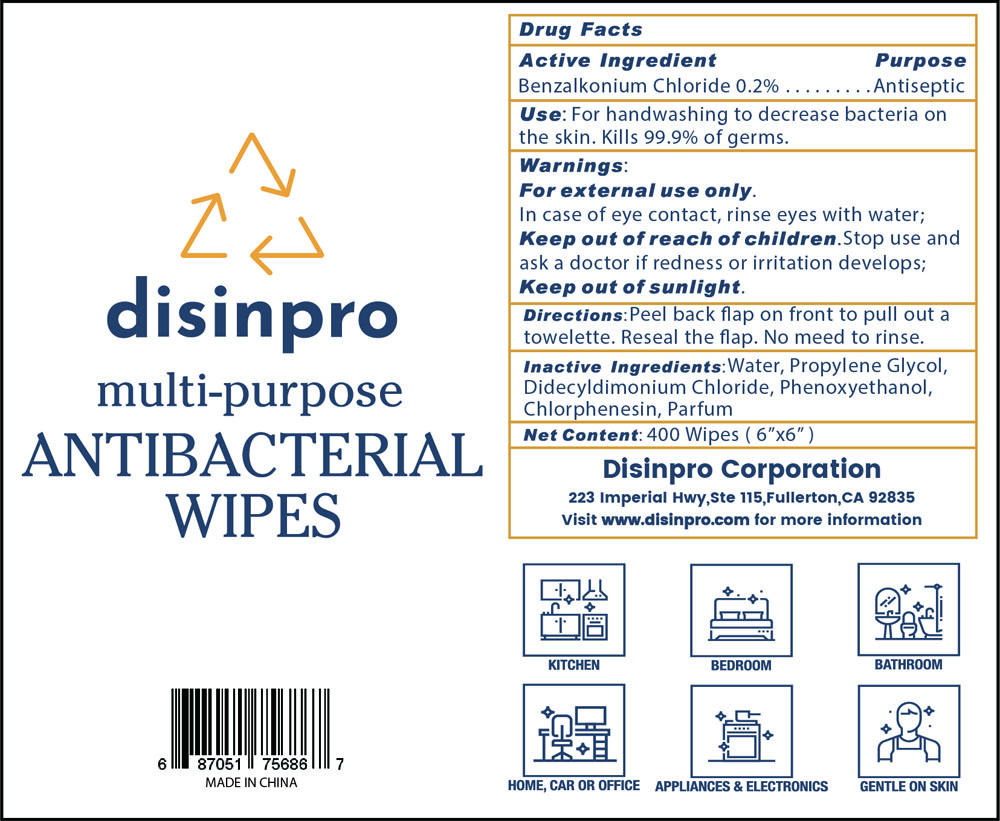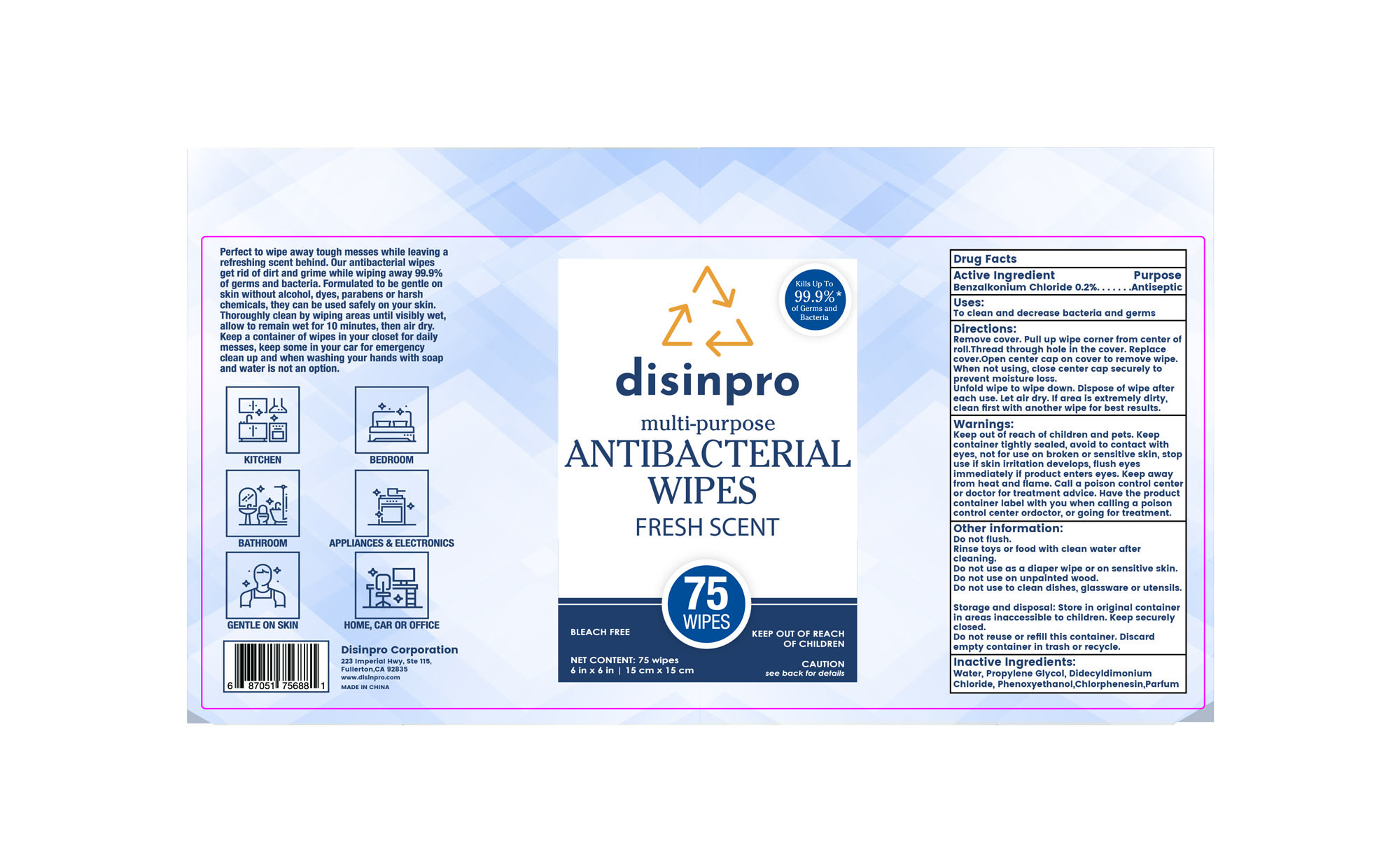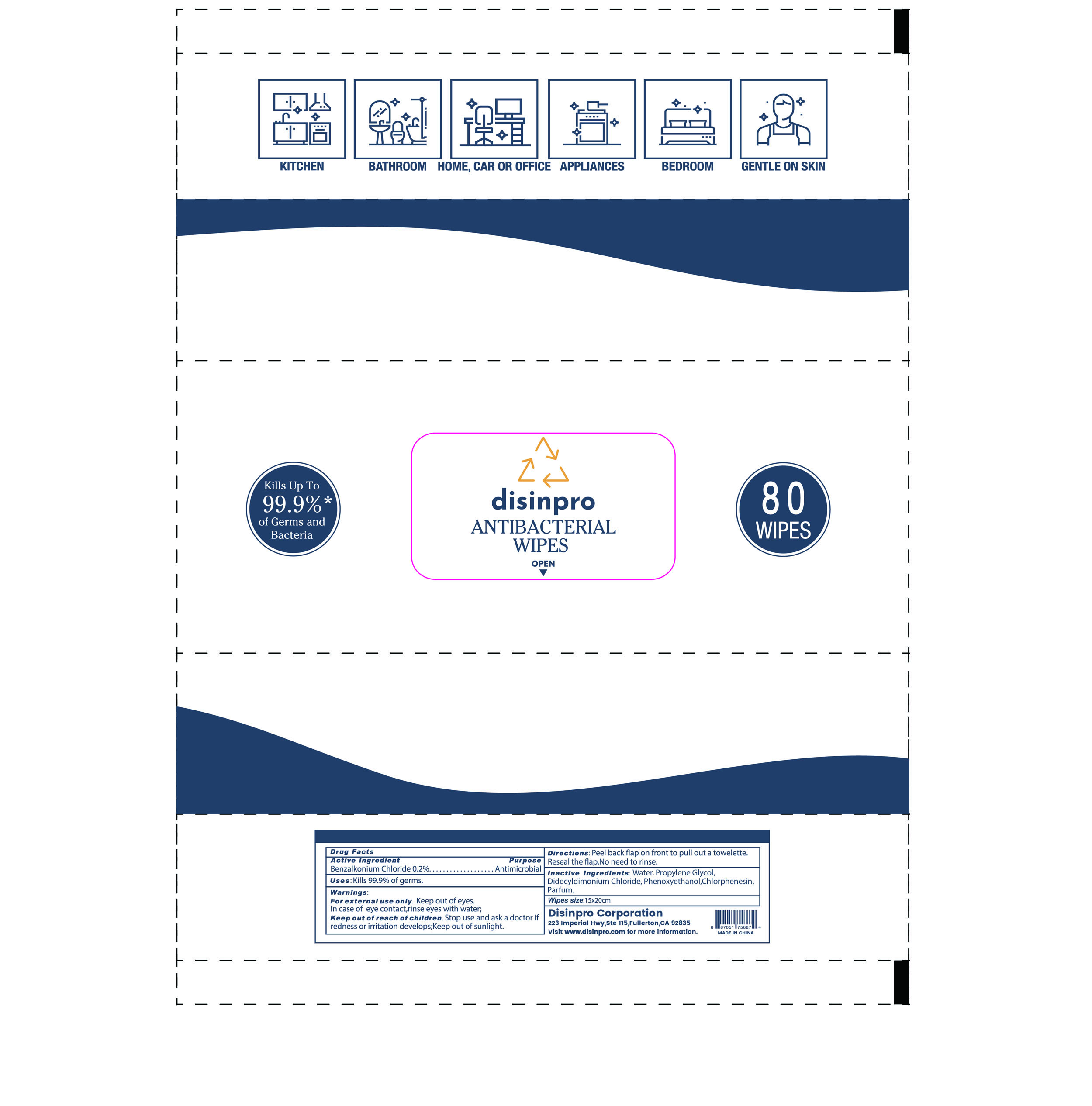 DRUG LABEL: disinpro ANTIBACTERIAL WIPES
NDC: 76635-008 | Form: CLOTH
Manufacturer: Hangzhou Glamcos Biotech CO.,LTD
Category: otc | Type: HUMAN OTC DRUG LABEL
Date: 20231123

ACTIVE INGREDIENTS: BENZALKONIUM CHLORIDE 0.2 g/100 g
INACTIVE INGREDIENTS: FRAGRANCE LAVENDER & CHIA F-153480; CHLORPHENESIN; DIDECYLDIMONIUM CHLORIDE; WATER; PROPYLENE GLYCOL; PHENOXYETHANOL

Active Ingredient

Benzalkonium Chloride 0.2%

Purpose

Antibacterial

Use

To clean and decrease bacteria and germs.

Warnings

Keep out of reach of children and pets.Keep container tightly sealed,avoid to contact with eyes,not for use on broken or sensitive skin,stop use if skin irritation develops,flush eyes immediately if product enters eyes.Keep awayfrom heat and flame.Call a poison control center or doctor for treatment advice.Have the product container label with you when calling a poison control center or doctor,or going for treatment.

Keep out of reach of children. If swallowed,get medical help or contact the poison control center immediately.

Directions

Remove cover.Pull up wipe corner from center of roll.Thread through hole in the cover.Replace cover. Open center cap on cover to remove wipe. When not using,close center cap securely to prevent moisture loss.
Unfold wipe to wipe down.Dispose wipe after each use.Let air dry.If area is extremely dirty,clean first with another wipe for best results.

OTHER SAFETY INFORMATION

Do not flush.
Rinse toys or food with clean water after cleaning.
Do not use as a diaper wipe or on sensitive skin.
Do not use on unpainted wood.
Do not use to clean dishes,glassware or utensils.
Storage and disposal: Store in original container in areas inaccessible to children.Keep securely closed.Do not reuse or refill this container.Discard empty container in trash or recycle.
Perfect to wipe away tough messes while leaving a refreshing scent behind. Our antibacterial wipes get rid of dirt and grime while wiping away 99.9% of germs and bacteria. Formulated to be gentle on skin without alcohol,dyes,parabens or harsh chemicals,they can be used safely on your skin. Thoroughly clean by wiping areas until visibly wet,allow to remain wet for 10 minutes,then air dry. Keep a container of wipes in your closet for daily messes,keep some in your car for emergency clean up and when washning your hands with soap and water is not an option.
233 Imperial Hwy,Ste 115,Fullerton,CA 92835
www.disinpro.com

Inactive Ingredients

Water，Propylene Glycol，DidecyldimoniumChloride，Phenoxyethanol， Chlorphenesin， Parfum

Package Label

NDC:76635-008-01

NDC:76635-008-02

NDC:76635-008-03

NDC:76635-008-04